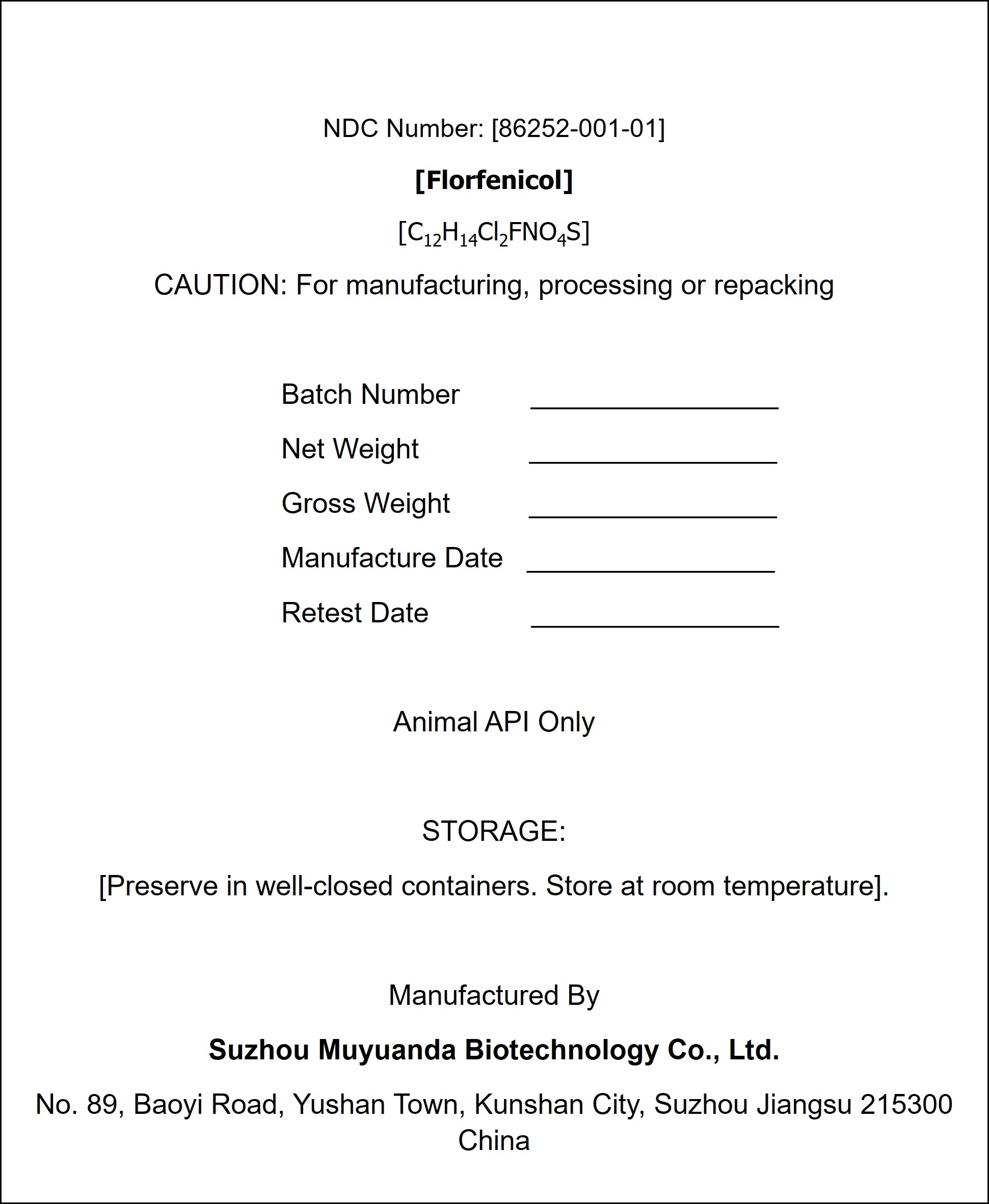 DRUG LABEL: Florfenicol
NDC: 86252-001 | Form: POWDER
Manufacturer: Suzhou Muyuanda Biotechnology Co., Ltd
Category: other | Type: BULK INGREDIENT - ANIMAL DRUG
Date: 20260222

ACTIVE INGREDIENTS: Florfenicol 1 mg/1 mg

PDP

NDC Number: [86252-001-01]
[Florfenicol]
[C12H14Cl2FNO4S]
CAUTION: For manufacturing, processing or repacking

Batch Number ________________
Net Weight ________________
Gross Weight ________________
Manufacture Date ________________
Retest Date ________________

Animal API Only

STORAGE:
[Preserve in well-closed containers. Store at room temperature].

Manufactured By
Suzhou Muyuanda Biotechnology Co., Ltd.
No. 89, Baoyi Road, Yushan Town, Kunshan City, Suzhou Jiangsu 215300 China